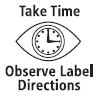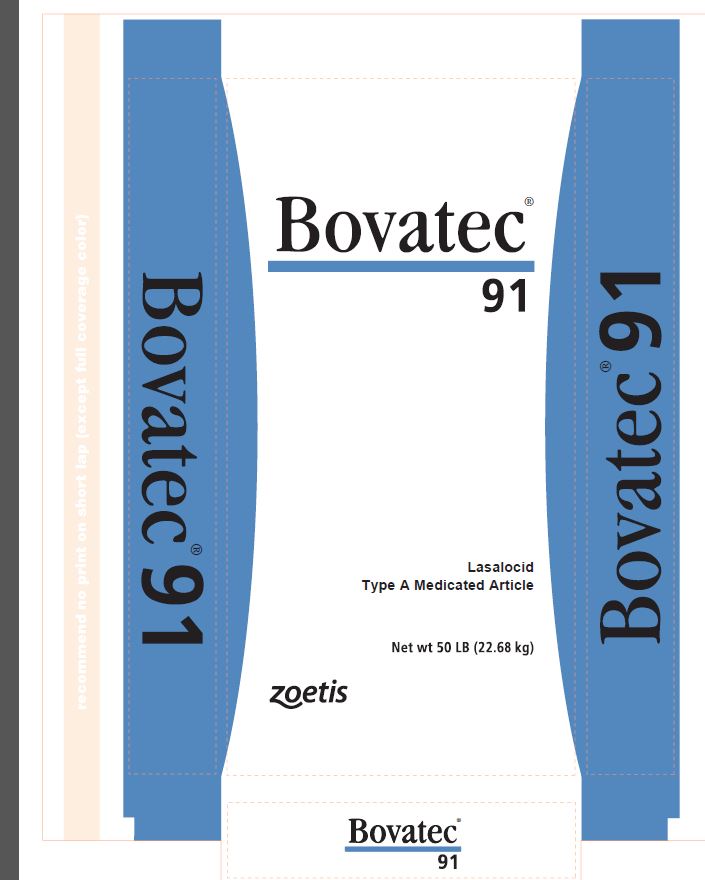 DRUG LABEL: Bovatec
NDC: 54771-1461 | Form: GRANULE
Manufacturer: Zoetis Inc.
Category: animal | Type: OTC TYPE A MEDICATED ARTICLE ANIMAL DRUG LABEL
Date: 20200625

ACTIVE INGREDIENTS: LASALOCID SODIUM 90.7 g/0.45 kg

Bovatec® 91

Lasalocid
Type A Medicated Article

Net wt 50 LB (22.68 kg)

Active ingredient

Each pound contains 90.7 grams (20%) of lasalocid (as lasalocid sodium activity) in a carrier suitable for incorporation in feed.

Important

Handling Information - Must be thoroughly mixed in feeds before use. When mixing and handling lasalocid Type A medicated articles, use protective clothing, impervious gloves and a dust mask. Avoid contact with eyes. Operators should wash hands thoroughly with soap and water after handling.

Mixing directions

This product should be further diluted in an intermediate blending step prior to mixing in the final feed. Do not feed undiluted.

1. Complete Feed

a. Intermediate blending: Mix 1 part of Bovatec 91 (Type A Medicated Article) with 17 parts of finely ground non-medicated feedstuffs to provide an intermediate preblend containing 5 grams of lasalocid per pound.
b. Using the 5 g/lb intermediate preblend, the following table would apply to the manufacture of complete feeds:

Intended lasalocid concentration in the complete feed |  | Add the following amounts of 5 grams per pound intermediate preblend per ton of complete feed mixed:
grams/ton | mg/lb | lbs/ton
10 | 5 | 2
15 | 7.5 | 3
30* | 15 | 6

* Maximum approved concentration for complete feeds for cattle fed in confinement for slaughter and sheep in confinement
c. Using the 5 g/lb intermediate preblend, the following table would apply to the manufacture of other complete feeds and supplements that do not require further mixing:

Daily feeding rate | Desired daily lasalocid intake | Add the following amounts of 5 grams per pound intermediate preblend per ton of feed or supplement mixed: | Lasalocid will be present in the feed or supplement at the following concentration:
lbs/head/day | mg/head/day | lbs/ton | grams/ton
1 | 60 | 24 | 120
1 | 200 | 80 | 400
1 | 300 | 120 | 600
2 | 60 | 12 | 60
2 | 200 | 40 | 200
2 | 300 | 60 | 300
3 | 60 | 8 | 40
3 | 200 | 26.7 | 133.5
3 | 300 | 40 | 200

2. Dry Supplement
a. Intermediate blending: Mix 1 part Bovatec 91 Type A Medicated Article with 3.5 parts of finely ground non-medicated feedstuffs to provide an intermediate preblend containing 20 grams of lasalocid per pound. For example, mix one 50 lb bag of Bovatec 91 Type A Medicated Article with 175 lbs of non-medicated feedstuffs.
b. Using the 20 g/lb intermediate preblend, the following table would apply to the manufacture of dry supplements:

Intended lasalocid concentration in the supplement |  | Add the following amounts of 20 grams per pound intermediate preblend per ton of supplement mixed:
grams/ton | mg/lb | lbs/ton
400 | 200 | 20
600 | 300 | 30
1000 | 500 | 50
1440 | 720 | 72
1600 | 800 | 80

c. Thoroughly mix supplement with sufficient non-medicated feedstuffs in accordance with the feeding rates listed in the use directions below.
3. Liquid Supplement Intended for Addition to Dry Feeds
a. Supplements with suspending agent(s) should be in a pH range of 4-8 and maintain physical stability for up to three months with a viscosity not less than 300 cps.
b. Conventional liquid supplements should be in a pH range of 4-8.
For liquid feeds stored in recirculating tank systems: Recirculate immediately prior to use for no less than 10 minutes, moving not less than 1 percent of the tank contents per minute from the bottom of the tank to the top. Recirculate daily as described even when not used.
For liquid feeds stored in mechanical, air, or other agitation-type tank systems: Agitate immediately prior to use for not less than 10 minutes, creating a turbulence at the bottom of the tank that is visible at the top. Agitate daily as described even when not used.

Use directions

Species | Dose | Indications for use
Cattle Fed in Confinement for Slaughter | 10-30 grams lasalocid per ton of total ration (90% dry matter) | For improved feed efficiency in cattle fed in confinement for slaughter, feed continuously to provide not less than 100 mg nor more than 360 mg per head per day.
Cattle Fed in Confinement for Slaughter
Cattle Fed in Confinement for Slaughter | 25-30 grams lasalocid per ton of total ration (90% dry matter) | For improved feed efficiency and increased rate of weight gain in cattle fed in confinement for slaughter, feed continuously to provide not less than 250 mg nor more than 360 mg per head per day.
Pasture Cattle – slaughter, stocker, feeder cattle, and dairy and beef replacement heifers | 60-300 mg lasalocid per head/day | For increased rate of weight gain. The drug must be contained in at least 1 pound of feed and fed continuously on a daily basis.
Pasture Cattle – slaughter, stocker, feeder cattle, and dairy and beef replacement heifers
Pasture Cattle – slaughter, stocker, feeder cattle, and dairy and beef replacement heifers | 60-300 mg lasalocid per head/day | For increased rate of weight gain, feed continuously on a free-choice basis. A medicated feed mill license is required when free-choice feed is manufactured using a proprietary formula and/or specifications. Free-choice feed formulations must be FDA-approved.
Pasture Cattle – slaughter, stocker, feeder cattle, and dairy and beef replacement heifers
Pasture Cattle – slaughter, stocker, feeder cattle, and dairy and beef replacement heifers |  | Daily lasalocid intakes in excess of 200 mg per head per day have not been shown to be more effective than 200 mg lasalocid per head per day.
Pasture Cattle – slaughter, stocker, feeder cattle, and dairy and beef replacement heifers
Pasture Cattle – slaughter, stocker, feeder cattle, and dairy and beef replacement heifers |  | NOTE: Coccidiosis may occur when young pasture cattle are co-mingled with adult cattle passing coccidial oocysts.
Cattle | 1 mg lasalocid per 2.2 lbs body weight/day | For control of coccidiosis caused by Eimeria bovis and E. zuernii in cattle up to 800 lbs. Hand feed continuously to provide not more than 360 mg per day.
Sheep | 20-30 grams lasalocid per ton of total ration (90% dry matter) | For prevention of coccidiosis caused by Eimeria ovina, E. crandallis, E. ovinoidalis (E. ninakohlyakimovae), E. parva, and E. intricata in sheep maintained in confinement. Feed continuously to provide not less than 15 mg nor more than 70 mg per head per day depending on body weight.

Caution

Animal Safety - Feeding undiluted or mixing errors may result in an excess lasalocid concentration which could be fatal to cattle and sheep. Do not allow horses or other equines access to Type A articles or Type B feeds containing lasalocid as ingestion may be fatal. Safety of lasalocid for use in unapproved species has not been established.

Withdrawal Periods and Residue Warnings

No withdrawal period is required when used according to labeling.
A withdrawal period has not been established for this product in pre-ruminating calves.
Do not use in calves to be processed for veal.

Store below 25°C (77°F), excursions permitted to 37°C (99°F).
Restricted drug (California) - Use only as directed. Not for human use.
Approved by FDA under NADA # 096-298

zoetis
Distributed by:
Zoetis Inc.
Kalamazoo, MI 49007

Net wt 50 LB (22.68 kg)

Made in USA

40030593